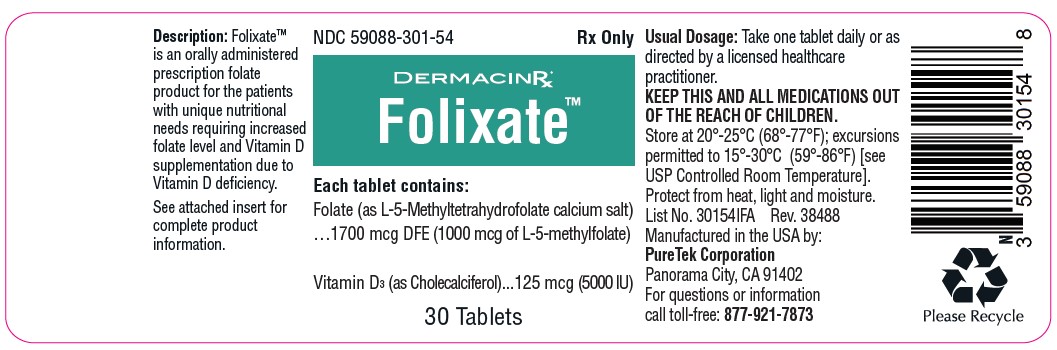 DRUG LABEL: Folixate
NDC: 59088-301 | Form: TABLET
Manufacturer: PureTek Corporation
Category: prescription | Type: HUMAN PRESCRIPTION DRUG LABEL
Date: 20231205

ACTIVE INGREDIENTS: LEVOMEFOLATE CALCIUM 1000 ug/1 1; VITAMIN D 125 ug/1 1
INACTIVE INGREDIENTS: LACTOSE MONOHYDRATE; SODIUM STARCH GLYCOLATE TYPE A; MAGNESIUM STEARATE; MICROCRYSTALLINE CELLULOSE; STEARIC ACID

Folixate™
(Folic Acid, Vitamin D3 Tablet)
Rx Only

DESCRIPTION

Folixate™ is an orally administered prescription folate product for the dietary management of patients with unique nutritional needs requiring increased folate level and Vitamin D supplementation due to Vitamin D deficiency.

Folixate™ should be administered under the supervision of a licensed healthcare practitioner.

Each tablet contains:
Folate (as L-5-Methyltetrahydrofolate calcium salt)......1700 mcg DFE
(1000 mcg of L-5-methylfolate)
Vitamin D3 (as Cholecalciferol)………....................125 mcg (5000 IU)

Each tablet contains the following inactive ingredients: Lactose Monohydrate, Magnesium Stearate, Microcrystalline Cellulose, Sodium Starch Glycolate, Vegetable Stearic Acid.

INDICATIONS AND USAGE

Folixate™ is indicated for dietary management of patients with unique nutritional needs requiring increased folate level and Vitamin D supplementation.

Folixate™ can be taken by women of childbearing age, pregnant women, and lactating and nonlactating mothers.

CLINICAL PHARMACOLOGY

The in vivo synthesis of the major biologically active metabolites of Vitamin D occurs in two steps. The first hydroxylation of ergocalciferol takes place in the liver (to 25-hydroxyvitamin D) and the second in the kidneys (to 1,25-dihydroxyvitamin D). Vitamin D metabolites promote the active absorption of calcium and phosphorus by the small intestine, thus elevating serum calcium and phosphate levels sufficiently to permit bone mineralization. Vitamin D metabolites also mobilize calcium and phosphate from bone and probably increase the reabsorption of calcium and perhaps also of phosphate by the renal tubules.

There is a time lag of 10 to 24 hours between the administration of Vitamin D and the initiation of its action in the body due to the necessity of synthesis of the active metabolites in the liver and kidneys. Parathyroid hormone is responsible for the regulation of this metabolism in the kidneys.

CONTRAINDICATIONS

This product is contraindicated in patients with a known hypersensitivity to any of the ingredients. Folixate™ is contraindicated in patients with hypercalcemia, malabsorption syndrome, abnormal sensitivity to the toxic effects of Vitamin D, and hypervitaminosis D.

WARNINGS AND PRECAUTIONS

Tell your doctor if you have: kidney problems, thyroid disease. This medication should be used as directed during pregnancy or while breast-feeding. Consult your doctor about the risks and benefits. Folate alone is improper therapy in the treatment of pernicious anemia and other megaloblastic anemias where Vitamin B12 is deficient. Folate in doses above 0.1 mg daily may obscure pernicious anemia in that hematologic remission can occur while neurological manifestations progress.

ADVERSE REACTIONS

Allergic sensitization has been reported following both oral and parenteral administration of folate.

You should call your doctor for medical advice about serious adverse events. To report adverse side effects or to obtain product information, contact PureTek Corporation, at 1-877-921-7873.

DOSAGE AND ADMINISTRATION

Take one tablet daily or as directed by a licensed healthcare practitioner.

HOW SUPPLIED

Folixate™ Tablets are supplied as round, light yellow tablets with one side scored, the other side plain and dispensed in child-resistant bottles of 30 tablets (NDC 59088-301-54).

* This product is a prescription-folate with or without other dietary ingredients that – due to increased folate levels (AUG 2, 1973 FR 20750), requires an Rx on the label because of increased risk associated with masking of B12 deficiency (pernicious anemia). Based on our assessment of the risk of obscuring pernicious anemia, this product requires licensed healthcare practitioner supervision, an Rx status, and a National Drug Code (NDC) or similarly-formatted product code, as required by pedigree reporting requirements and supply-chain control as well as in some cases, for insurance-reimbursement applications.

All prescriptions using this product shall be pursuant to state statutes as applicable. This is not an Orange Book product. This product may be administered only under a physician’s supervision. There are no implied or explicit claims on therapeutic equivalence.

STORAGE

KEEP THIS AND ALL MEDICATIONS OUT OF THE REACH OF CHILDREN.

Store at 20°-25°C (68°-77°F); excursions permitted to 15°-30°C (59°-86°F) [see USP Controlled Room Temperature]. Protect from
heat, light and moisture.

Tamper Evident: Do not use if seal is broken or missing.